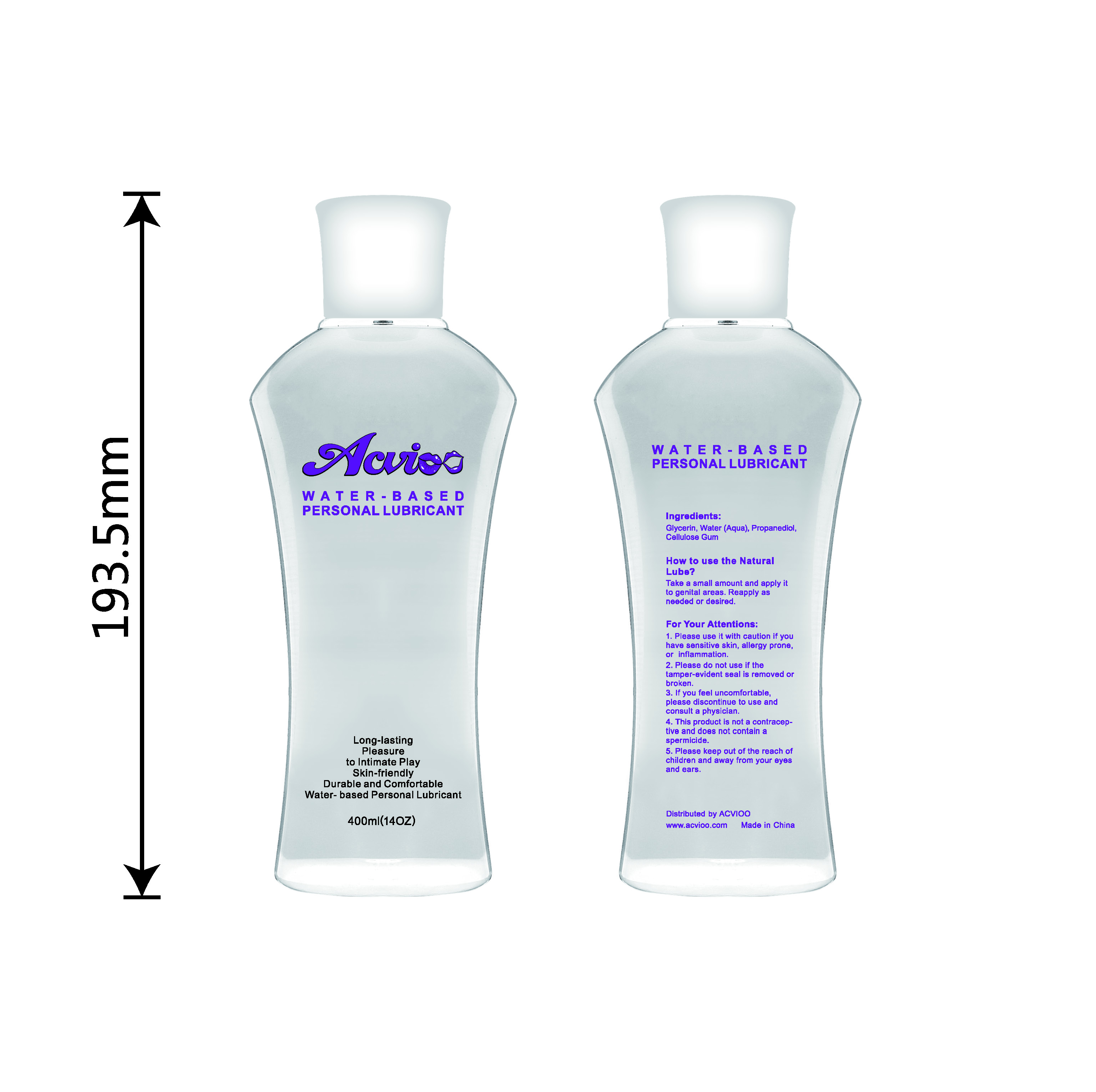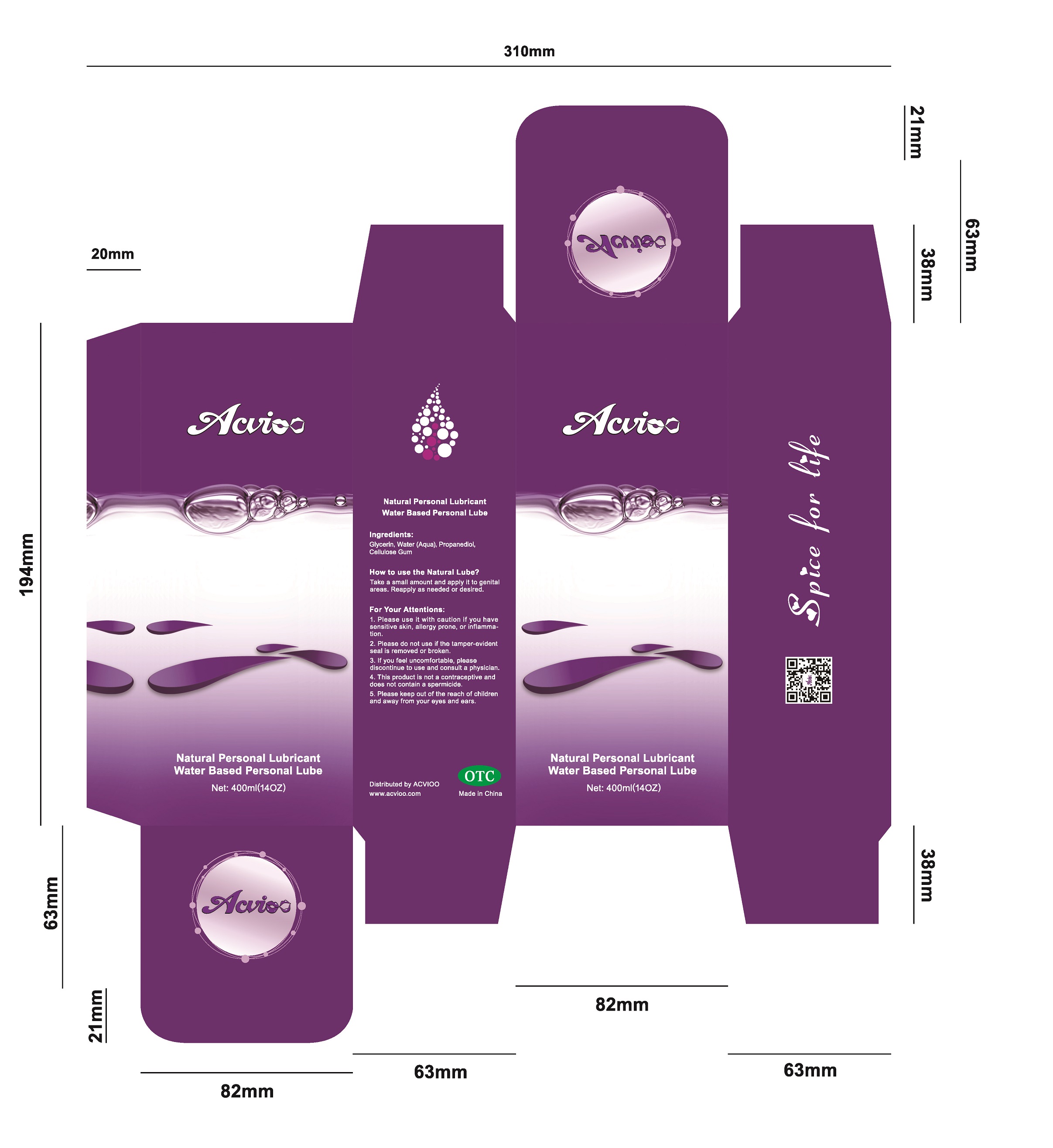 DRUG LABEL: Water-based Personal Lubricant, ACVIOO 001
NDC: 71847-2215 | Form: OIL
Manufacturer: Shenzhen Dikailong Technology Ltd
Category: otc | Type: HUMAN OTC DRUG LABEL
Date: 20180507

ACTIVE INGREDIENTS: BUTYLENE GLYCOL 80 g/400 mL
INACTIVE INGREDIENTS: HYDROXYETHYL CELLULOSE (280 MPA.S AT 2%) 6.4 mL/400 mL; WATER 310.08 mL/400 mL; PHENOXYETHANOL 1.2 mL/400 mL; POLYETHYLENE GLYCOL 300000 2 mL/400 mL; CHLORPHENESIN 0.32 mL/400 mL

Water-based Personal Lubricant, ACVIOO 001 (400mL)

Active ingredient

butylene glycol (20%): 80g/package or 80mL/package

Inactive ingredient

water (77.52%): 310.08mL/package

hydroxyethylcellulose (1.6%): 6.4mL/package

polyethylene glycol 300000 (0.5%): 2mL/package

phenoxyethanol (0.3%): 1.2mL/package

chlorphenesin (0.08%): 0.32mL/package

Purpose

It can achieve higher lubricantion, longer lubrication time and less dosage.

This product is not a contraceptive and does not contain a spermicide.

When using

Virginal dryness and/or intimate sexual activity.

This product is not a contraceptive and does not contain a spermicide.

Do not use when wound or skin infection.

It should be cautiously used if you are kind of allergic constitution or you have inflammation.
Do not use if quality seal on the opening of the tube is broken or missing.
Do not use if tamper-evident seal is removed or broken.

Stop use

If irritation or discomfort occurs, discontinue the use and consult a physician.
Very slippery on surfaces, clean spills immediately.

Ask doctor

If irritation or discomfort occurs, discontinue the use and consult a physician.

Ask doctor/pharmacist when you current use other drugs.

Keep out of reach of children and away from eyes and ears.

Questions

Please contact us when you have any questions.

Pregnancy or breast feeding

Pregnant or breast feeding women shall follow doctor advice.

Indications & usage

ACVIOO 001 is a water-based personal lubricant, for penile and/or vaginal application, intended to lubricate and moisturize, to enhance the ease and comfort of intimate sexual activity, help relieve virginal dryness, and supplement to the body's natural lubricant.

Apply a small amount to genital areas. Reapply as needed or desired.

Dosage & administration

One bottle of 400mL in one package.

Dosage forms & strengths

The lubricant is like oil form.

A small amount one time, or reapply as needed or desired.

The active ingredient strength is 20%.

Warnings

If irritation or discomfort occurs, discontinue the use and consult a physician.
Very slippery on surfaces, clean spills immediately.

This product is not a contraceptive and does not contain a spermicide.

Package label. Principal display panel

---

Container Label

---

---

Package Label

---